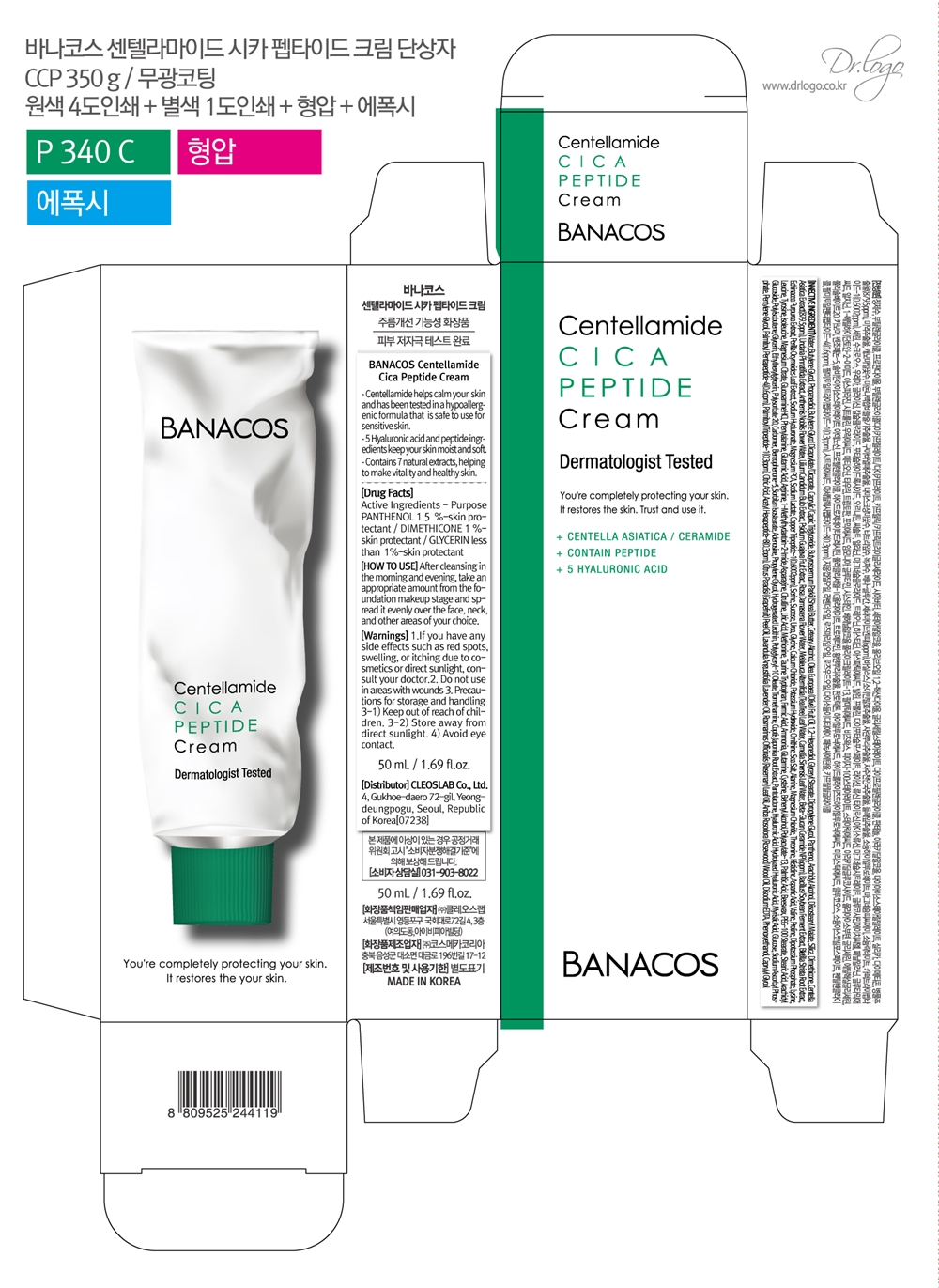 DRUG LABEL: BANACOS Centellamide Cica Peptidecream
NDC: 79540-303 | Form: CREAM
Manufacturer: Cleoslab Co., Ltd
Category: otc | Type: HUMAN OTC DRUG LABEL
Date: 20211219

ACTIVE INGREDIENTS: PANTHENOL 1.5 g/100 mL; GLYCERIN 0.1159 g/100 mL; DIMETHICONE 1 g/100 mL
INACTIVE INGREDIENTS: MEDIUM-CHAIN TRIGLYCERIDES 4 mL/100 mL; GRAPEFRUIT OIL 0.045 mL/100 mL; SORBITAN ISOSTEARATE 0.04 mL/100 mL; PROPYLENE GLYCOL 0.032 mL/100 mL; TROMETHAMINE 0.03 mL/100 mL; EDETATE DISODIUM ANHYDROUS 0.0206 mL/100 mL; SODIUM ASCORBYL PHOSPHATE 0.0012 mL/100 mL; CURDLAN 0.0004 mL/100 mL; MAGNESIUM CITRATE 0.00000000062 mL/100 mL; TAURINE 0.00000000024 mL/100 mL; TRYPTOPHAN 0.0000000002 mL/100 mL; CYSTEINE 0.000000000076 mL/100 mL; BUTYLENE GLYCOL 12.19978 mL/100 mL; PEG-100 STEARATE 0.48 mL/100 mL; OLIVE OIL 2.5 mL/100 mL; MAGNESIUM PIDOLATE 0.00000002628 mL/100 mL; PHENYLALANINE 0.000000000552 mL/100 mL; CREATININE 0.0000000005 mL/100 mL; CITRIC ACID MONOHYDRATE 0.000035 mL/100 mL; PALMITOYL TRIPEPTIDE-1 0.00003 mL/100 mL; ACETYL HEXAPEPTIDE-8 0.00003 mL/100 mL; SUCROSE 0.00000000838 mL/100 mL; UREA 0.000000007 mL/100 mL; ALANINE 0.0000000042 mL/100 mL; HISTIDINE 0.0000000018 mL/100 mL; ASPARTIC ACID 0.000000001456 mL/100 mL; VALINE 0.000000001348 mL/100 mL; POTASSIUM PHOSPHATE, DIBASIC 0.000000000916 mL/100 mL; LYSINE 0.000000000828 mL/100 mL; LEUCINE 0.000000000744 mL/100 mL; GLUTAMIC ACID 0.000000000548 mL/100 mL; ARGININE 0.00000000054 mL/100 mL; METHIONINE 0.00000000028 mL/100 mL; PALMITOYL PENTAPEPTIDE-4 0.00006 mL/100 mL; FORMIC ACID 0.00000000012 mL/100 mL; AMMONIA 0.0000000001 mL/100 mL; GLUTAMINE 0.00000000008 mL/100 mL; PALMITIC ACID 0.55 mL/100 mL; SILICON DIOXIDE 1 mL/100 mL; HYALURONIC ACID 0.02 mL/100 mL; CAPRYLYL GLYCOL 0.00045 mL/100 mL; CHAMAEMELUM NOBILE FLOWER OIL 0.0002 mL/100 mL; PREZATIDE COPPER 0.00006002 mL/100 mL; BUTYROSPERMUM PARKII (SHEA) BUTTER UNSAPONIFIABLES 3.499965 mL/100 mL; ARACHIDYL GLUCOSIDE 0.4375 mL/100 mL; CETOSTEARYL ALCOHOL 2.5 mL/100 mL; 1,2-HEXANEDIOL 2.07147 mL/100 mL; DIPROPYLENE GLYCOL 2 g/100 mL; TEA TREE OIL 0.094 mL/100 mL; ETHYLHEXYLGLYCERIN 0.050051 mL/100 mL; CARBOMER HOMOPOLYMER, UNSPECIFIED TYPE 0.05 mL/100 mL; POLYSORBATE 20 0.05 mL/100 mL; BENZOPHENONE-5 0.05 mL/100 mL; ADENOSINE 0.04 mL/100 mL; LAVENDER OIL 0.035 mL/100 mL; HYDROGENATED SOYBEAN LECITHIN 0.0305 mL/100 mL; POLYGLYCERYL-10 OLEATE 0.03 mL/100 mL; COPTIS JAPONICA ROOT 0.02941 mL/100 mL; MYRISTIC ACID 0.01 mL/100 mL; ANHYDROUS DEXTROSE 0.0075 mL/100 mL; BLETILLA STRIATA BULB 0.00175 mL/100 mL; CALCIUM CHLORIDE 0.00000000538 mL/100 mL; MAGNESIUM CHLORIDE 0.00000000234 mL/100 mL; PROLINE 0.000000000996 mL/100 mL; TYROSINE 0.000000000692 mL/100 mL; GLUCOSAMINE HYDROCHLORIDE 0.0000000006 mL/100 mL; CITRULLINE 0.000000000456 mL/100 mL; URIC ACID 0.0000000004 mL/100 mL; PANTOLACTONE, (R)- 0.02 mL/100 mL; SERINE 0.00000000992 mL/100 mL; ARACHIDYL ALCOHOL 1.35 mL/100 mL; PROPANEDIOL 6.94 mL/100 mL; BUTYLENE GLYCOL DICAPRYLATE/DICAPRATE 5 mL/100 mL; YELLOW WAX 0.8 mL/100 mL; TRICAPRIN 4.062 mL/100 mL; ROSEWOOD OIL 0.0002 mL/100 mL; ISOLEUCINE 0.00000000064 mL/100 mL; ASPARAGINE 0.000000000472 mL/100 mL; HYALURONATE SODIUM 0.0201 mL/100 mL; LILIUM CANDIDUM BULB 0.02 mL/100 mL; ROSEMARY OIL 0.0198 mL/100 mL; ORNITHINE 0.000000005 mL/100 mL; THREONINE 0.000000002052 mL/100 mL; SHEA BUTTER 3.499965 mL/100 mL; ROSA DAMASCENA FLOWER OIL 0.0995 mL/100 mL; GUAVA 0.01 mL/100 mL; PENTYLENE GLYCOL 0.0005 mL/100 mL; SODIUM LACTATE 0.00000002506 mL/100 mL; POTASSIUM HYDROXIDE 0.00000000512 mL/100 mL; CERAMIDE NP 0.0006 mL/100 mL; ECHINACEA PURPUREA 0.00175 mL/100 mL; PERILLA FRUTESCENS LEAF 0.00175 mL/100 mL; SOYBEAN 0.00175 mL/100 mL; SEA SALT 0.00100000482 mL/100 mL; TEA LEAF OIL 0.001 mL/100 mL; PHENOXYETHANOL 0.0003 mL/100 mL; DOCOSANOL 0.7 mL/100 mL; WATER 45.928908852364 mL/100 mL; GLYCERYL MONOSTEARATE 2.02 mL/100 mL; DIISOSTEARYL MALATE 1 mL/100 mL; CENTELLA ASIATICA 0.08795 mL/100 mL; UNDARIA PINNATIFIDA 0.05 mL/100 mL; STEARIC ACID 0.44 mL/100 mL; POLYISOBUTYLENE (1000 MW) 0.28 mL/100 mL

Cream

BANACOS CENTELLAMIDE CICA PEPTIDE CREAM

GLYCERIN
PANTHENOL
DIMETHICONE
DIPROPYLENE GLYCOL
CYSTEINE

stop use and ask a doctor

Take care not to get into the eye.

If you have any side effects such as red spots, swelling or tiching due to cosmetic or direct sunlight, consult your doctor.

PURPOSE

PURPOSE [OTC - PURPOSE SECTION] EDIT

skinprotect

Warning

For external use only

Keep away from fire of flame

Do not spray on clothes because it can stain.

Be caeful not to get into your eyes, and if so wash thoroughly with water

Keep out of reach of children.

indication

sprinkle evenly on your face

Direction

After cleansing in the morning and evening take an appropriate amount from the foundation makeup stage and spread it evenly over the face, neck, and other areas of your choice.

do not use in areas with wounds.

avoid eye contact

inactive

SILICON DIOXIDE
BUTYROSPERMUM PARKII (SHEA) BUTTER UNSAPONIFIABLES
ARACHIDYL GLUCOSIDE
CETOSTEARYL ALCOHOL
1,2-HEXANEDIOL
ARACHIDYL ALCOHOL
PROPANEDIOL
BUTYLENE GLYCOL DICAPRYLATE/DICAPRAT
YELLOW WAX

label

79540-303-01